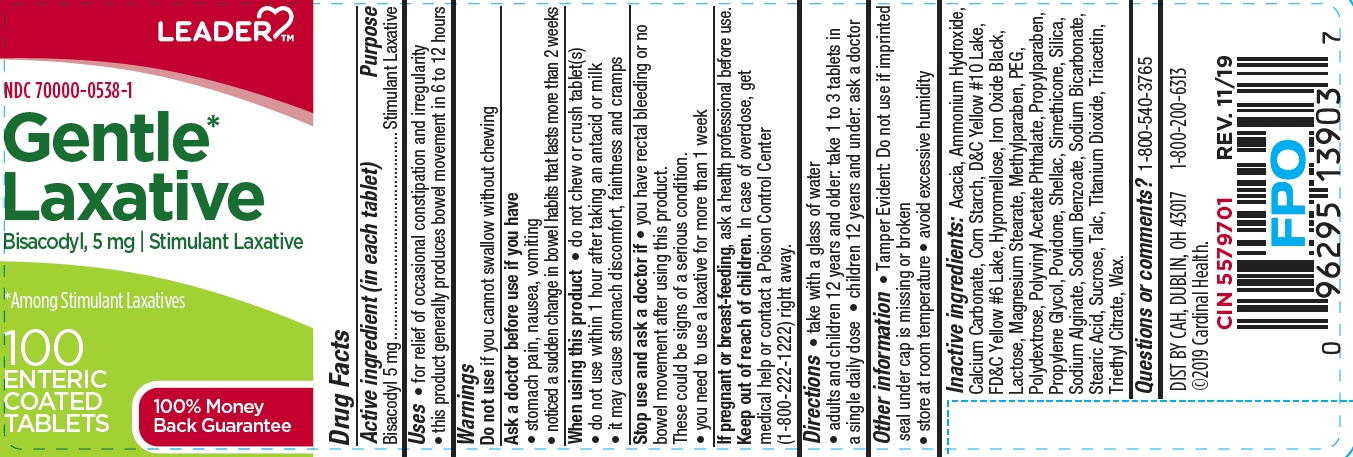 DRUG LABEL: Gentle Laxative
NDC: 70000-0538 | Form: TABLET
Manufacturer: CARDINAL HEALTH
Category: otc | Type: HUMAN OTC DRUG LABEL
Date: 20231206

ACTIVE INGREDIENTS: BISACODYL 5 mg/1 1
INACTIVE INGREDIENTS: AMMONIA; CALCIUM CARBONATE; ACACIA; CARNAUBA WAX; STARCH, CORN; D&C YELLOW NO. 10; FD&C YELLOW NO. 6; HYPROMELLOSES; FERROSOFERRIC OXIDE; LACTOSE MONOHYDRATE; MAGNESIUM STEARATE; METHYLPARABEN; POLYDEXTROSE; POLYETHYLENE GLYCOL, UNSPECIFIED; POLYVINYL ACETATE PHTHALATE; PROPYLPARABEN; PROPYLENE GLYCOL; POVIDONE; SHELLAC; DIMETHICONE; SILICON DIOXIDE; SODIUM ALGINATE; SODIUM BENZOATE; SODIUM BICARBONATE; STEARIC ACID; SUCROSE; TALC; TITANIUM DIOXIDE; TRIACETIN; TRIETHYL CITRATE

ldr441

Active ingredient (in each tablet)

Bisacodyl 5 mg

Purpose

Stimulant Laxative

Uses

- for relief of occasional constipation and irregularity
- this product generally produces bowel movement in 6 to 12 hour

Warnings

Do not use if you cannot swallow without chewing

Ask a doctor before use if you have

- stomach pain, nausea, vomiting
- noticed a sudden change in bowel habits that lasts more than 2 weeks

When using this product

- do not chew or crush tablet(s)
- do not use within 1 hour after taking an antacid or milk
- it may cause stomach discomfort, faintness and cramps

Stop use and ask a doctor if

- you have rectal bleeding or no bowel movement after using this product.

These could be signs of a serious condition.

- you need to use a laxative for more than 1 week

If pregnant or breast-feeding, ask a health professional before use.

Keep out of reach of children. In case of overdose, get medical help or contact a Poison Control Center (1-800-222-1222) right away.

Directions

- take with a glass of water
- adults and children 12 years and older: take 1 to 3 tablets in a single daily dose
- children 12 years and under: ask a doctor

Other information

- Tamper Evident: Do not use if imprinted seal under cap is missing or broken
- store at room temperature
- avoid excessive humidity

Inactive ingredients

Acacia, Ammonium Hydroxide, Calcium Carbonate, Corn Starch, D and C Yellow NO. 10 Lake, FD and C Yellow NO. 6 Lake, Hypromellose, Iron Oxide Black, Lactose, Magnesium Stearate, Methylparaben, PEG, Polydextrose, Polyvinyl Acetate Phthalate, Propylparaben, Propylene Glycol, Povidone, Shellac, Simethicone, Silica, Sodium Alginate, Sodium Benzoate, Sodium Bicarbonate, Stearic Acid, Sucrose, Talc, Titanium Dioxide, Triacetin, Triethyl Citrate, Wax